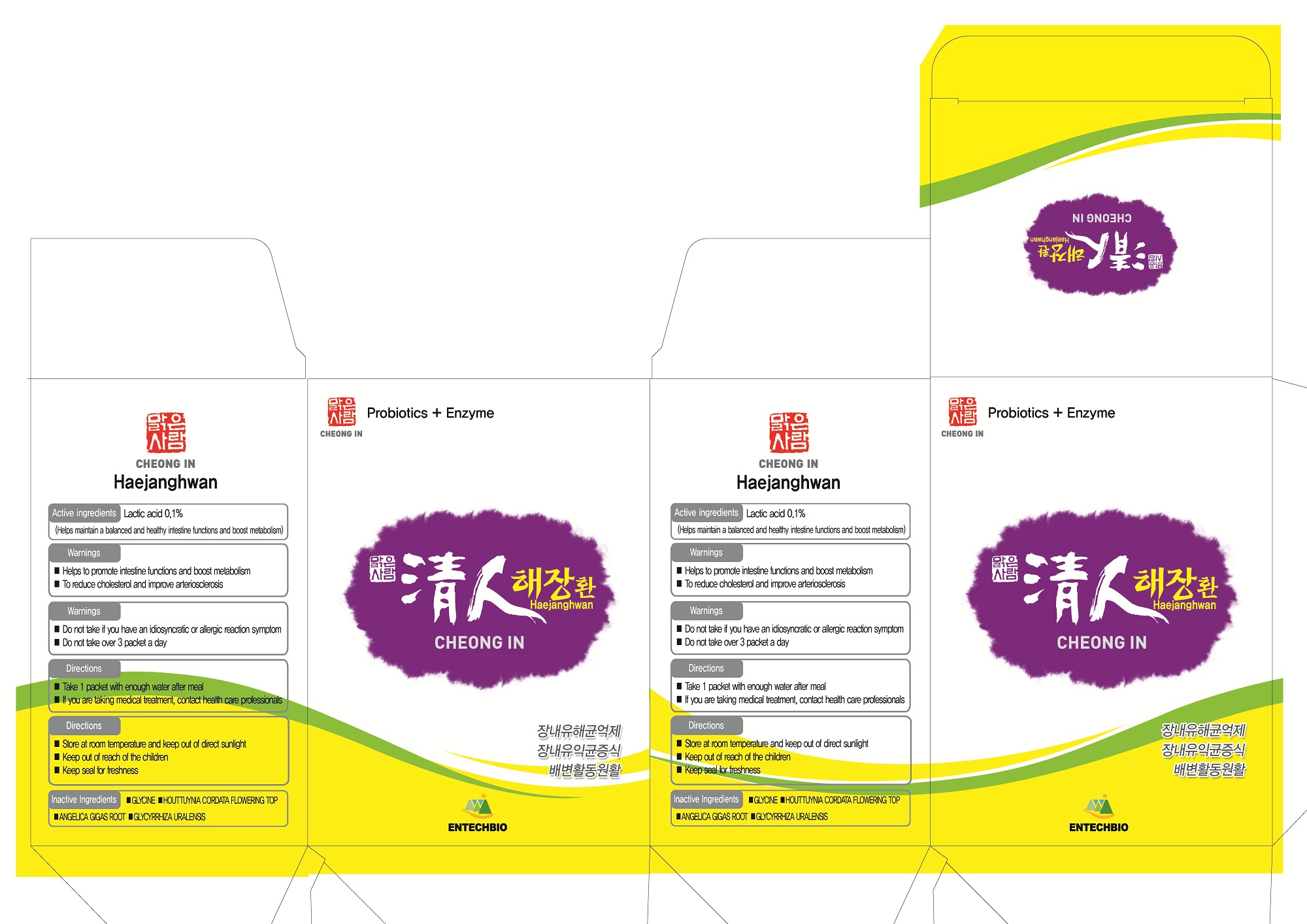 DRUG LABEL: Cheongin Haejanghwan
NDC: 75863-2001 | Form: PELLET
Manufacturer: Entechbio Co., Ltd
Category: otc | Type: HUMAN OTC DRUG LABEL
Date: 20110218

ACTIVE INGREDIENTS: LACTIC ACID 0.001 g/1 g
INACTIVE INGREDIENTS: GLYCINE; HOUTTUYNIA CORDATA FLOWERING TOP; ANGELICA GIGAS ROOT; GLYCYRRHIZA URALENSIS

Drug Facts

active ingredient: lactic acid (lactobacillus casei, lactobacillus bifidus)

inactive ingredient: GLYCINE, HOUTTUYNIA CORDATA FLOWERING TOP, ANGELICA GIGAS ROOT, GLYCYRRHIZA URALENSIS

PURPOSE

helps to promote intestine functions and boost metabolism
to reduce cholesterol and improve arteriosclerosis

keep out of reach of the children

INDICATIONS AND USAGE

take 1 packet with enough water after meal

WARNINGS

do not take if you have an idiosyncratic of allergic reaction symptom
do not take over 3 packet a day

DOSAGE AND ADMINISTRATION

take continuously even if you feel improvement of physical constitution